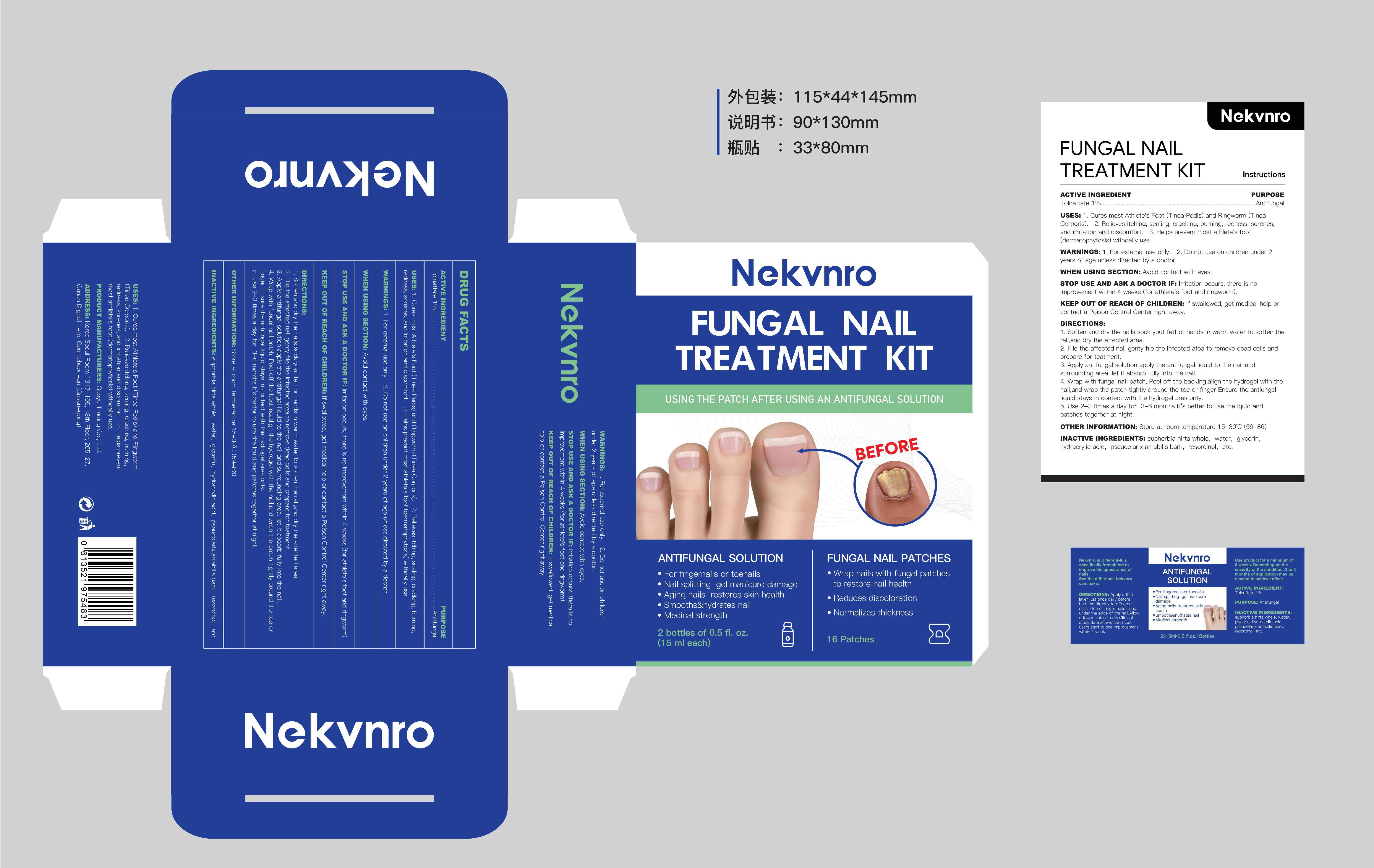 DRUG LABEL: Nekvnro FUNGAL NAIL TREATMENT Kit
NDC: 84844-019 | Form: LIQUID
Manufacturer: Guoyu Trading Co., Ltd.
Category: otc | Type: HUMAN OTC DRUG LABEL
Date: 20250325

ACTIVE INGREDIENTS: TOLNAFTATE 1 g/100 mL
INACTIVE INGREDIENTS: EUPHORBIA HIRTA WHOLE; RESORCINOL; HYDRACRYLIC ACID; GLYCERIN; PSEUDOLARIX AMABILIS BARK; WATER

84844-019

Active Ingredient

Tolnaftate 1%

Purpose

Antifungal

Use

1，Cures most Athlete's Foot (Tinea Pedis) and Ringworm (Tinea Corporis).

2，Relieves itching, scaling, cracking, burning, redness, sorenes, and irritation and discomfort.
3，Helps prevent most athlete's foot (dermatophytosis) withdaily use.

Warnings

1，For external use only.
2，Do not use on children under 2 years of age unless directed by a doctor.

Do not use

on children under 2 years of age unless directed by a doctor.

When Using

section
avoid contact with eyes.

Stop Use

and ask a doctor if irritation occurs, there is no improvement within 4 weeks (for athlete's foot and ringworm).

Ask Doctor

irritation occurs, there is no improvement within 4 weeks (for athlete's foot and ringworm).

Keep Oot Of Reach Of Children

If swallowed, get medical help or contact a Poison Control Center right away.

Directions

1，soften and dry the nalls sock yout fett or hands in warm water to soften the rall,and dry the affected area
2，file the affected nail genty file the lnfected atea to remove dead cells and prepare for teatment
3，apply antifungal solution apply the antifungal liquid to the nail and surrounding area. let it absorb fully into the nail
4，wrap with fungal nail patch
Peel off the backing.align the hydrogel with the nail,and wrap the patch tightly around the toe or finger Ensure the antiungal liquid stays in contect with the hydrogel ares onty
5，use 2-3 times a day for 3-6 months lt‘s better to use the lquid and patches togerher at night.

Other information

Store at room temperature 15-30℃ (59-86)

Inactive ingredients

euphorbia hirta whole，water，glycerin，hydracrylic acid，pseudolarix amabilis bark，resorcinol，etc.